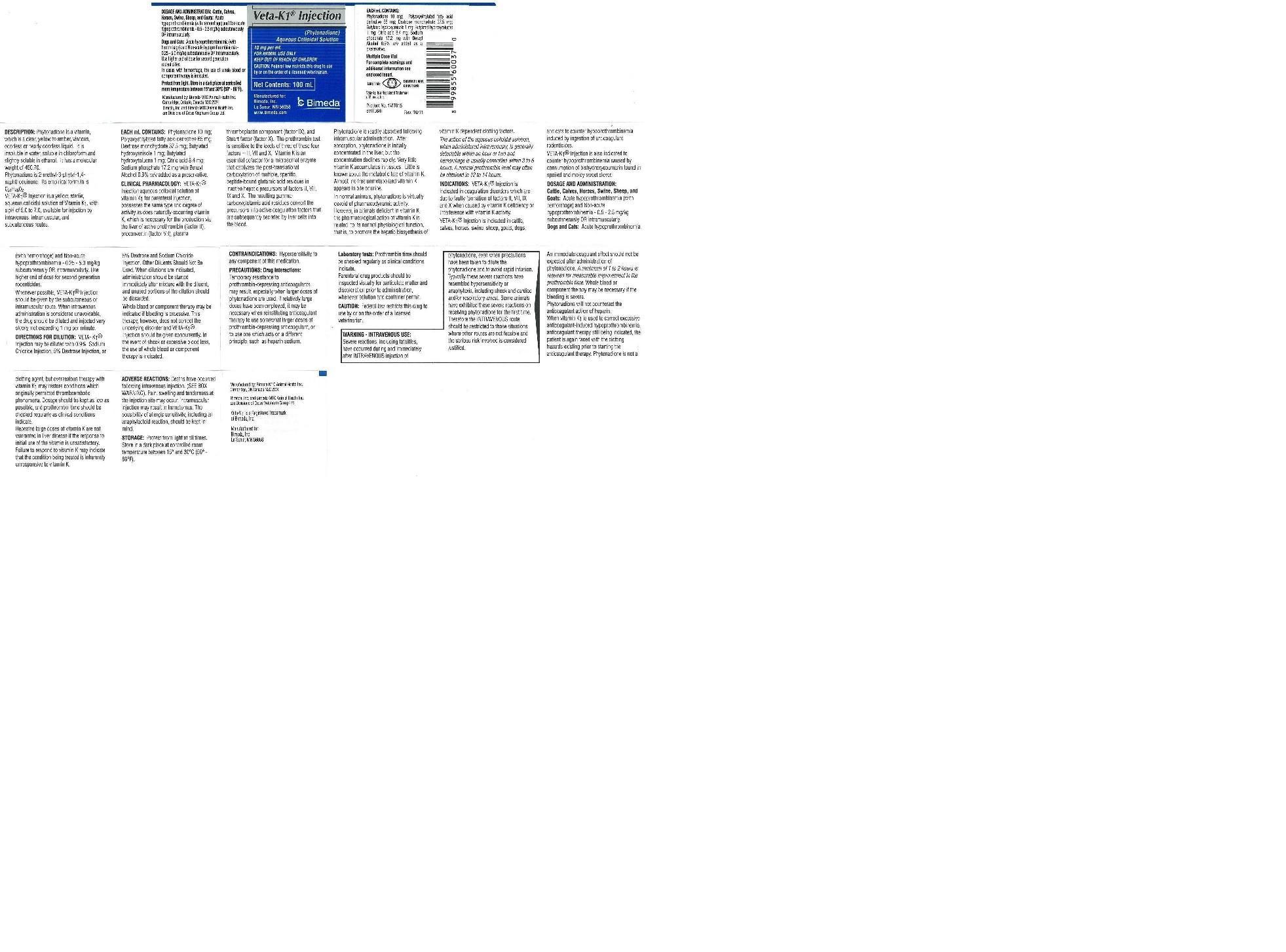 DRUG LABEL: Veta-K1
NDC: 61133-6003 | Form: SOLUTION
Manufacturer: Bimeda Inc.
Category: animal | Type: PRESCRIPTION ANIMAL DRUG LABEL
Date: 20181207

ACTIVE INGREDIENTS: PHYTONADIONE 10 mg/1 mL

DESCRIPTION

Veta-K1® Injection

(phytonadione)

Aqueous Colloidal Solution

10 mg/mL

FOR ANIMAL USE ONLY

KEEP OUT OF REACH OF CHILDREN

CAUTION: Federal law restricts this drug to use by or on the order of a lincensed veterinarian

Net Contents: 100 mL

Multiple Dose Vial

For complete warnings and additional information see enclosed insert.

DESCRIPTION: Phytonadione is a vitamin, which is a clear, yellow to amber, viscous, odorless or nearly odorless liquid. It is insoluble in water, soluble in chloroform and slightly soluble in ethanol. It has a molecular weight of 450.70.

Phytonadione is 2-methyl-3-phytyl-1, 4-naphthoquinone. Its empirical formula is C31H46O2.

Veta-K1® Injection is a yellow, sterile, aqueous colloidal solution of vitamin K1, with a pH of 5.0 to 7.0, available for injection by the intravenous, intramuscular and subcutaneous routes.

EACH mL CONTAINS: Phytonadione 10 mg; Polyoxyethylated fatty acid derivative 65 mg; Dextrose monohydrate 37.5 mg; Butylated hydroxyanisole 1 mg; Butylated hydroxytoluene 1 mg; Citric acid 8.4 mg; Sodium phosphate 17.2 mg; with Benzyl Alcohol 0.9% w/v added as a preservative.

CLINICAL PHARMACOLOGY:

Veta-K1® Injection aqueous colloidal solution of vitamin K1 for parenteral injection, possesses the same type and degree of activity as does naturally-occurring vitamin K, which is necessary for the production via the liver of active prothrombin (factor II), proconvertin (factor VII), plasma thromboplastin component (factor IX), and Stuart factor (factor X). The prothrombin test is sensitive to the levels of three of these four factors-II, VII, and X.

Vitamin K is an essential cofactor for a microsomal enzyme that catalyzes the post-translational carboxylation of multiple, specific, peptide-bound glutamic acid residues in inactive hepatic precursors of factors II, VII, IX, and X. The resulting gamma-carboxy-glutamic acid residues convert the precursors into active coagulation factors that are subsequently secreted by liver cells into the blood.

Phytonadione is readily absorbed following intramuscular administration. After absorption, phytonadione is initially concentrated in the liver, but the concentration declines rapidly. Very little vitamin K accumulates in tissues. Little is known about the metabolic fate of vitamin K. Almost no free unmetabolized vitamin K appears in bile or urine.

In normal animals and humans, phytonadione is virtually devoid of pharmacodynamic activity. However, in animals and humans deficient in vitamin K, the pharmacological action of vitamin K is related to its normal physiological function, that is, to promote the hepatic biosynthesis of vitamin K dependent clotting factors.

The action of the aqueous colloidal solution, when administered intravenously, is generally detectable within an hour or two and hemorrhage is usually controlled within 3 to 6 hours. A normal prothrombin level may often be obtained in 12 to 14 hours.

INDICATIONS AND USAGE

INDICATIONS: Veta-K1® Injection is indicated in coagulation disorders which are due to faulty formation of factors II, VII, IX and X when caused by vitamin K deficiency or interference with vitamin K activity.

Veta-K1® Injection is also indicated in cattle, calves, horses, swine, sheep, goats, dogs, and cats to counter hypoprothrombinemia induced by ingestion of anticoagulant rodenticides. Veta-K1® Injection is also indicated to counter hypoprothrombinemia caused by consumption of bishydroxycoumarin found in a spoiled and moldy sweet clover.

DOSAGE AND ADMINISTRATION: Cattle, Calves, Horses, Swine, Sheep, and Goats: Acute hypoprothrombinemia (with hemorrhage) and Non-acute hypoprothrombinemia - 0.5 - 2.5 mg/kg subcutaneously OR intramuscularly.

Dogs and Cats: Acute hypoprothrombinemia (with hemorrhage) and Non-acute hypoprothrombinemia - 0.25 - 5.0 mg/kg subcutaneously OR intramuscularly. Use higher end of dose for second generation rodenticides.

Whenever possible, Veta-K1® Injection should be given by the subcutaneous or intramuscular route. When intravenous administration is considered unavoidable, the drug should be diluted and injected very slowly, not exceeding 1 mg per minute.

DIRECTIONS FOR DILUTION: Veta-K1® Injection may be diluted with 0.9% Sodium Chloride Injection, 5% Dextrose Injection, or 5% Dextrose and Sodium Chloride Injection. Other Diluents Should Not Be Used. When dilutions are indicated, administration should be started immediately after mixture with the diluent, and unused portions of the dilution should be discarded.

Whole blood or component therapy may be indicated if bleeding is excessive. This therapy, however, does not correct the underlying disorder and Veta-K1® Injection should be given concurrently. In the event of shock or excessive blood loss, the use of whole blood component therapy is indicated.

CONTRAINDICATIONS:

Hypersensitivity to any component of this medication

PRECAUTIONS:

Drug Interactions: Temporary resistance to prothrombin-depressing anticoagulants may result, especially when larger doses of phytonadione are used. If relatively large doses have been employed, it may be necessary when reinstituting anticoagulant therapy to use somewhat larger doses of the prothrombin-depressing anticoagulant, or to use one which acts on a different principle, such as heparin sodium.

Laboratory Tests: Prothrombin time should be checked regularly as clinical conditions indicate.

Parenteral drug products should be inspected visually for particulate matter and discoloration prior to administration, whenever solution and container permit.

CAUTION: Federal law restricts this drug to use by or on the order of a lincensed veterinarian.

WARNING:

WARNING - INTRAVENOUS USE: Severe reactions, including fatalities, have occurred during and immediately after the INTRAVENOUS injection of phytonadione, even when precautions have been taken to dilute the phytonadione and to avoid rapid infusion. Typically these severe reactions have resembled hypersensitivity or anaphylaxis, including shock and cardiac and/or respiratory arrest. Some animals have exhibited these severe reactions on receiving phytonadione for the first time. Therefore, the INTRAVENOUS route should be restricted to those situations where other routes are not feasible and the serious risk involved is considered justified.

An immediate coagulant effect should not be expected after administration of phytonadione. A minimum of 1 to 2 hours is required for measurable improvement in the prothrombin time. Whole blood or component therapy may also be necessary if bleeding is severe.

Phytonadione will not counteract the anticoagulant action of heparin.

When vitamin K1 is used to correct excessive anticoagulant-induced hypoprothrombinemia, anticoagulant therapy still being indicated, the patient is again faced with the clotting hazards existing prior to starting the anticoagulant therapy. Phytonadione is not a clotting agent, but overzealous therapy with vitamin K1 may restore conditions which originally permitted thromboembolic phenomena. Dosage should be kept as low as possible, and prothrombin time should be checked regularly as clinical conditions indicate.

Repeated large doses of vitamin K are not warranted in liver disease if the response to initial use of the vitamin is unsatisfactory. Failure to respond to vitamin K may indicate that the condition being treated is inherently unresponsive to vitamin K.

ADVERSE REACTIONS

ADVERSE REACTIONS: Deaths have occured following intravenous injection. (SEE BOX WARNING). Pain, swelling, and tenderness at the injection site may occur. Intramuscular injection may result in hematomas. The possibility of allergic sensitivity, including an anaphylactoid reaction, should be kept in mind.

STORAGE AND HANDLING

STORAGE: Protect from light at all times. Store in a dark place at controlled room temperature between 15° and 30° C (59° - 86° F).